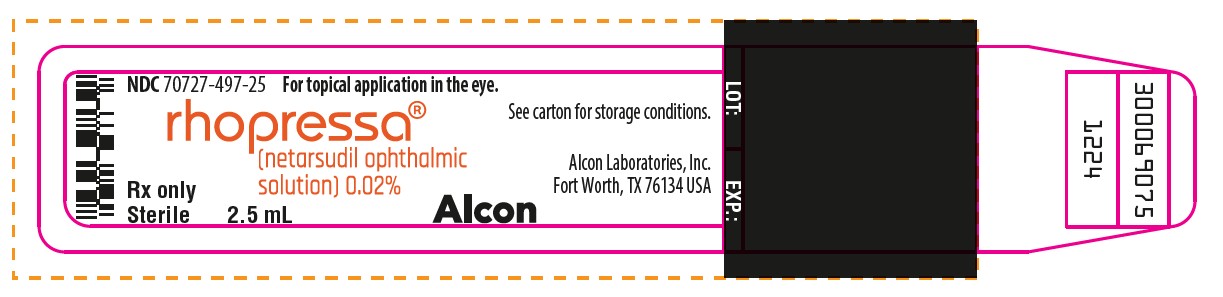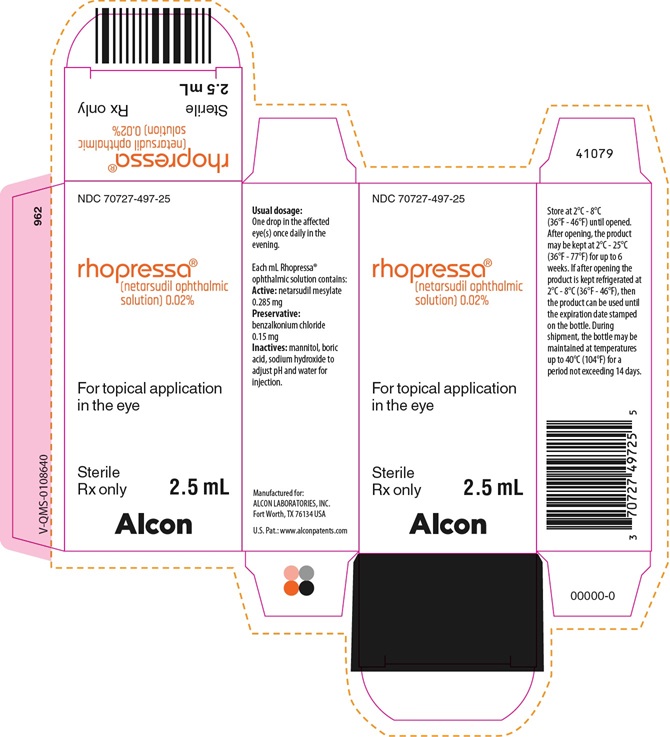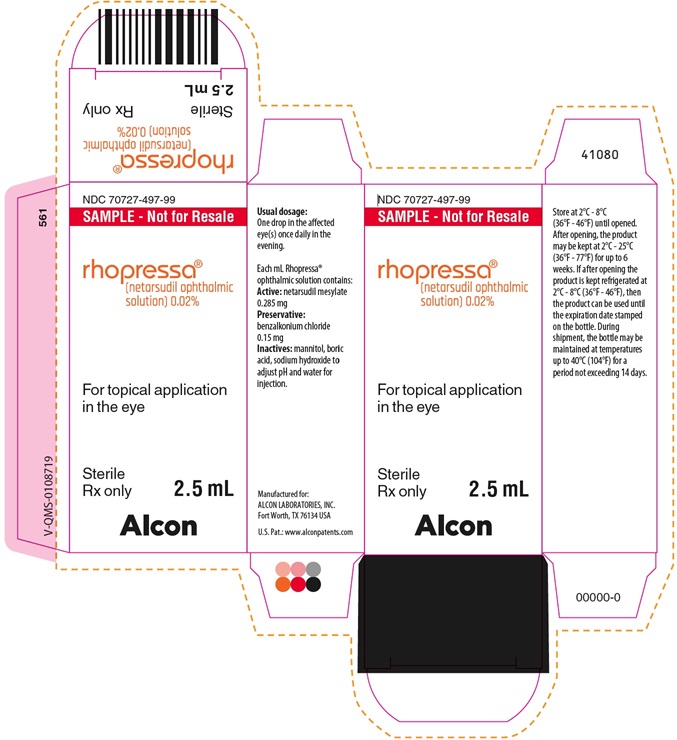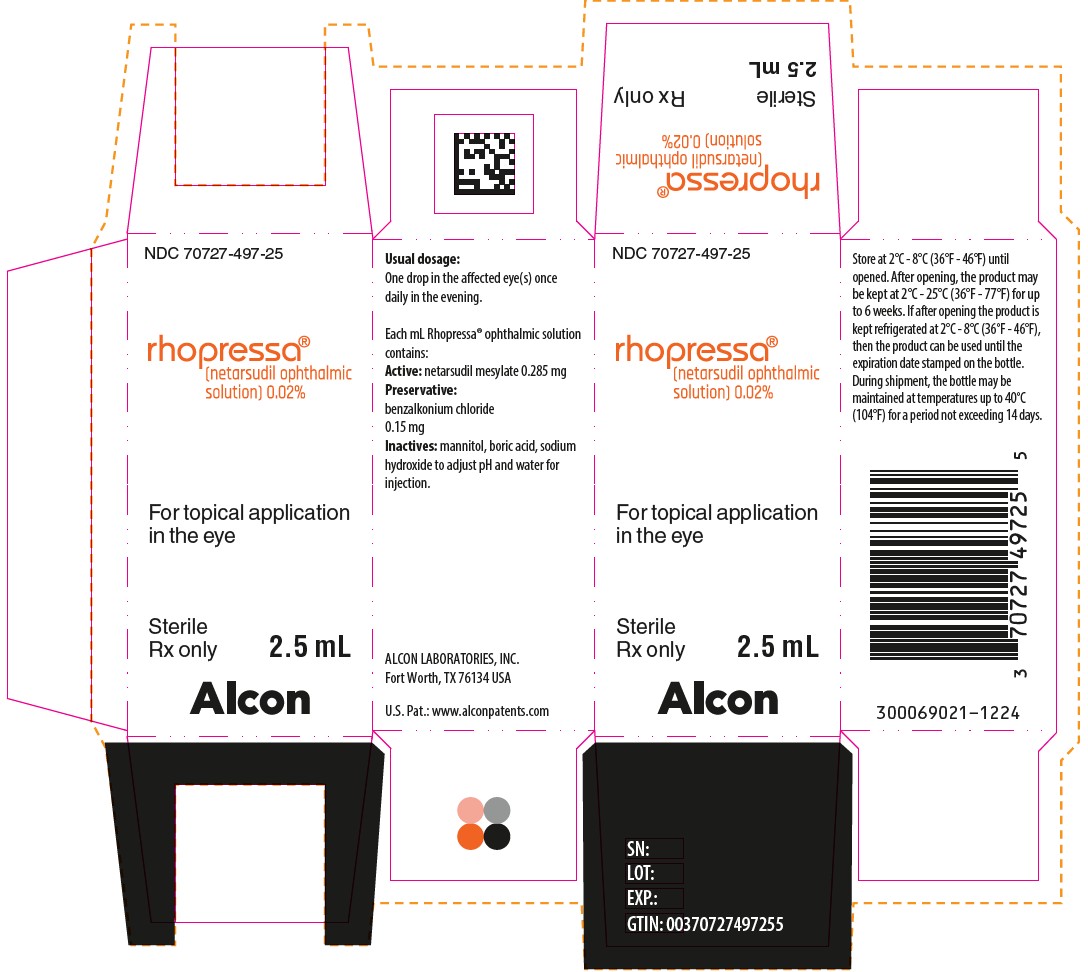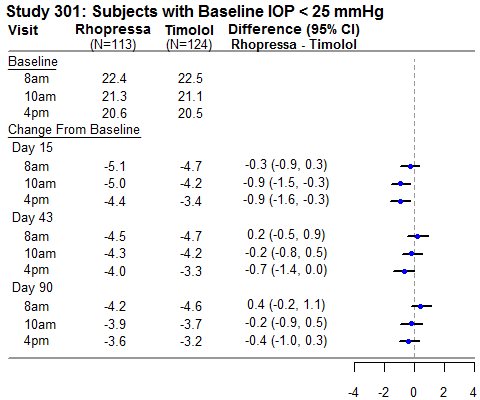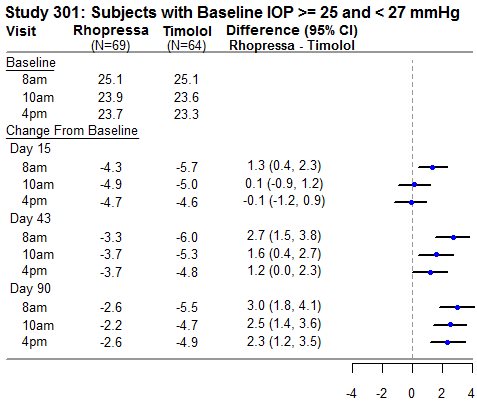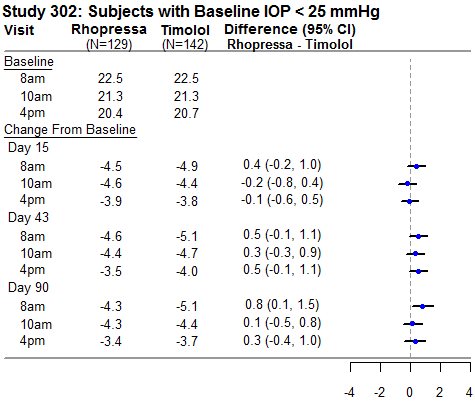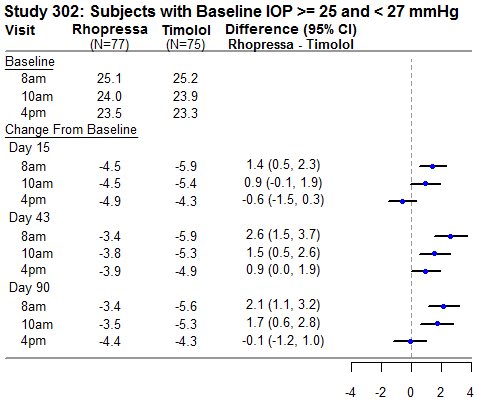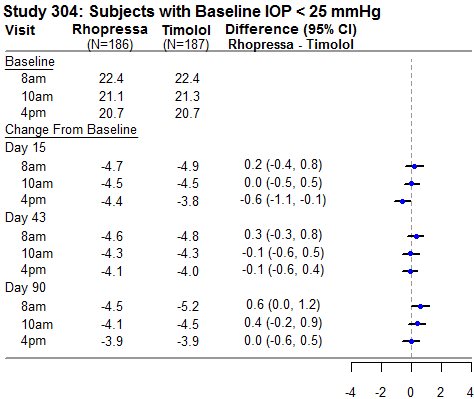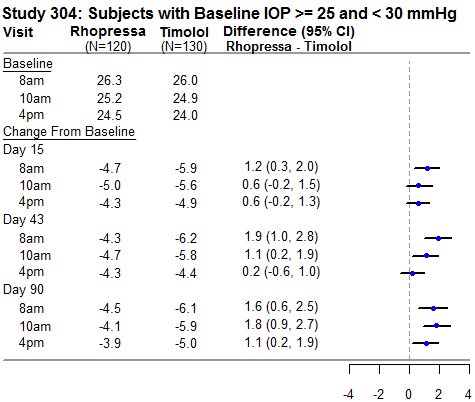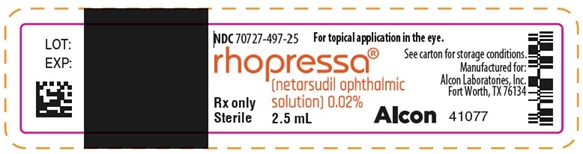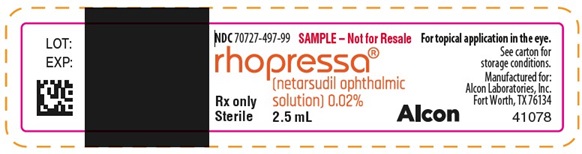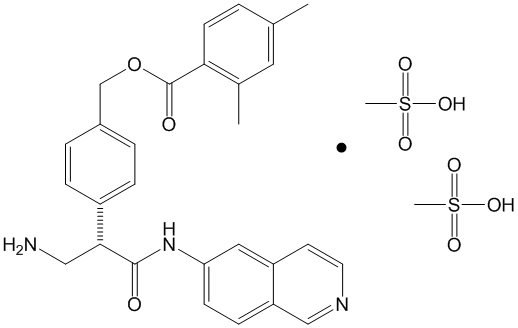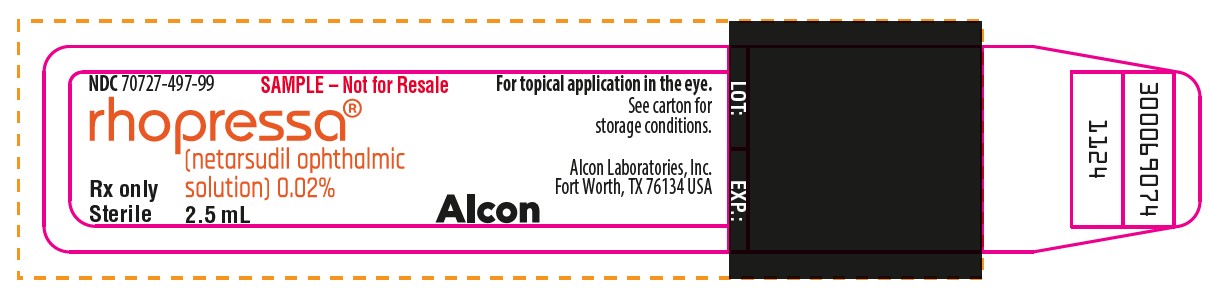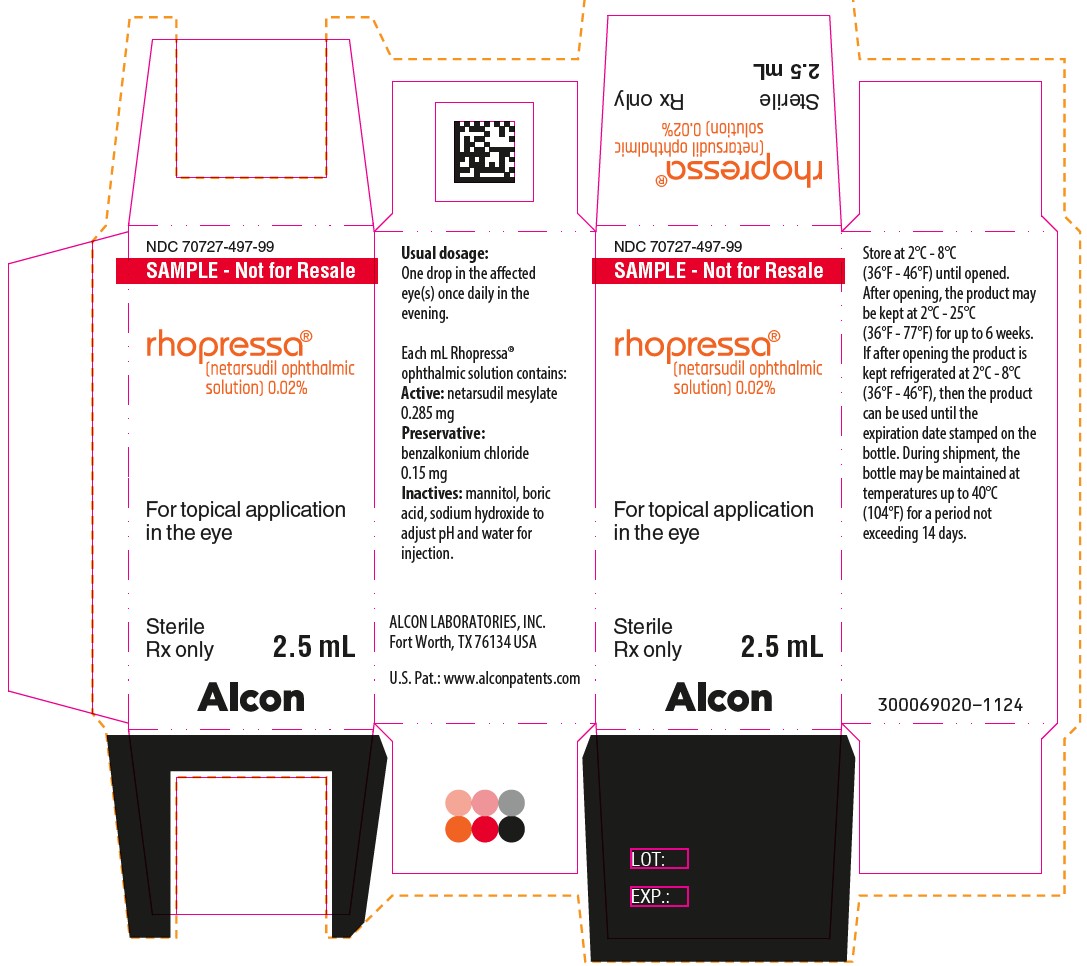 DRUG LABEL: Rhopressa
NDC: 70727-497 | Form: SOLUTION/ DROPS
Manufacturer: Alcon Laboratories, Inc.
Category: prescription | Type: HUMAN PRESCRIPTION DRUG LABEL
Date: 20260120

ACTIVE INGREDIENTS: NETARSUDIL MESYLATE 0.200 mg/1 mL
INACTIVE INGREDIENTS: BENZALKONIUM CHLORIDE; MANNITOL; BORIC ACID; SODIUM HYDROXIDE; WATER

HIGHLIGHTS OF PRESCRIBING INFORMATION

These highlights do not include all the information needed to use RHOPRESSA® safely and effectively. See full prescribing information for RHOPRESSA®.
RHOPRESSA® (netarsudil ophthalmic solution) 0.02%, for topical ophthalmic use
Initial U.S. Approval: 2017

1 INDICATIONS AND USAGE

RHOPRESSA® is a Rho kinase inhibitor indicated for the reduction of elevated intraocular pressure in patients with open-angle glaucoma or ocular hypertension. (1)

2 DOSAGE AND ADMINISTRATION

One drop into the affected eye(s) once daily in the evening. (2)

3 DOSAGE FORMS AND STRENGTHS

Ophthalmic solution containing netarsudil 0.02%. (3)

4 CONTRAINDICATIONS

None. (4)

RECENT MAJOR CHANGES

Warnings and Precautions, Epithelial Corneal Edema (5.1) 9/2024

6 ADVERSE REACTIONS

The most common adverse reaction is conjunctival hyperemia (53%). Other common adverse reactions, approximately 20% include: corneal verticillata, instillation site pain, and conjunctival hemorrhage. (6.1)

To report SUSPECTED ADVERSE REACTIONS, contact Alcon Laboratories, Inc. at 1‑800-757-9195, or FDA at
1-800-FDA-1088 or www.fda.gov/medwatch.

FULL PRESCRIBING INFORMATION

1 INDICATIONS AND USAGE

RHOPRESSA is indicated for the reduction of elevated intraocular pressure (IOP) in patients with open-angle glaucoma or ocular hypertension.

2 DOSAGE AND ADMINISTRATION

The recommended dosage is one drop in the affected eye(s) once daily in the evening.

If one dose is missed, treatment should continue with the next dose in the evening. Twice a day dosing is not well tolerated and is not recommended. If RHOPRESSA is to be used concomitantly with other topical ophthalmic drug products to lower IOP, administer each drug product at least 5 minutes apart [see Patient Counseling Information (17)].

3 DOSAGE FORMS AND STRENGTHS

Ophthalmic solution containing netarsudil 0.02% (0.2 mg/mL).

4 CONTRAINDICATIONS

None.

5 WARNINGS AND PRECAUTIONS

5.1 Epithelial Corneal Edema

Epithelial corneal edema, described as honeycomb or bullous, has been reported in some patients with pre-existing corneal stromal edema or following ocular procedures that could affect corneal endothelial function. Epithelial corneal edema typically resolves upon discontinuation of RHOPRESSA. Advise patients to notify their physician if they experience eye pain or decreased vision while using RHOPRESSA [see Adverse Reactions (6.2) and Patient Counselling Information (17)].

5.2 Bacterial Keratitis

There have been reports of bacterial keratitis associated with the use of multiple-dose containers of topical ophthalmic products. These containers had been inadvertently contaminated by patients who, in most cases, had a concurrent corneal disease or a disruption of the ocular epithelial surface [see Patient Counseling Information (17)].

5.3 Use with Contact Lenses

Contact lenses should be removed prior to instillation of RHOPRESSA and may be reinserted 15 minutes following its administration.

6 ADVERSE REACTIONS

6.1 Clinical Trials Experience

Because clinical studies are conducted under widely varying conditions, adverse reaction rates observed in the clinical studies of a drug cannot be directly compared to rates in the clinical studies of another drug and may not reflect the rates observed in practice.

The most common ocular adverse reaction observed in controlled clinical studies with RHOPRESSA dosed once daily was conjunctival hyperemia which was reported in 53% of patients. Six percent of patients discontinued therapy due to conjunctival hyperemia. Other common (approximately 20%) ocular adverse reactions reported were: corneal verticillata, instillation site pain, and conjunctival hemorrhage. Instillation site erythema, corneal staining, blurred vision, increased lacrimation, erythema of eyelid, and reduced visual acuity were reported in 5-10% of patients.

Corneal Verticillata

Corneal verticillata occurred in approximately 20% of the patients in controlled clinical studies. The corneal verticillata seen in RHOPRESSA-treated patients were first noted at 4 weeks of daily dosing. This reaction did not result in any apparent visual functional changes in patients. Most corneal verticillata resolved upon discontinuation of treatment.

6.2 Postmarketing Experience

The following adverse reactions have been identified during postmarketing use of RHOPRESSA. Because these reactions are reported voluntarily from a population of uncertain size, it is not always possible to reliably estimate their frequency or establish a causal relationship to drug exposure.

Eye disorders: Epithelial corneal edema has been reported in some patients with pre-existing corneal stromal edema or following ocular procedures (that could affect corneal endothelial function) [see Warnings and Precautions (5.1)].

8 USE IN SPECIFIC POPULATIONS

8.1 Pregnancy

Risk Summary

There are no available data on RHOPRESSA use in pregnant women to inform any drug associated risk; however, systemic exposure to netarsudil from ocular administration is low [see Clinical Pharmacology (12.3)]. Intravenous administration of netarsudil to pregnant rats and rabbits during organogenesis did not produce adverse embryofetal effects at clinically relevant systemic exposures [see Data].

Data

Animal Data

Netarsudil administered daily by intravenous injection to rats during organogenesis caused abortions and embryofetal lethality at doses ≥0.3 mg/kg/day (126-fold the plasma exposure at the recommended human ophthalmic dose [RHOD], based on Cmax). The no-observed-adverse-effect-level (NOAEL) for embryofetal development toxicity was 0.1 mg/kg/day (40-fold the plasma exposure at the RHOD, based on Cmax).

Netarsudil administered daily by intravenous injection to rabbits during organogenesis caused embryofetal lethality and decreased fetal weight at 5 mg/kg/day (1480-fold the plasma exposure at the RHOD, based on Cmax). Malformations were observed at ≥3 mg/kg/day (1330-fold the plasma exposure at the RHOD, based on Cmax), including thoracogastroschisis, umbilical hernia and absent intermediate lung lobe. The NOAEL for embryofetal development toxicity was 0.5 mg/kg/day (214-fold the plasma exposure at the RHOD, based on Cmax).

8.2 Lactation

Risk Summary

There are no data on the presence of RHOPRESSA in human milk, the effects on the breastfed infant, or the effects on milk production. However, systemic exposure to netarsudil following topical ocular administration is low [see Clinical Pharmacology (12.3)], and it is not known whether measurable levels of netarsudil would be present in maternal milk following topical ocular administration.

The developmental and health benefits of breastfeeding should be considered along with the mother’s clinical need for RHOPRESSA and any potential adverse effects on the breast-fed child from RHOPRESSA.

8.4 Pediatric Use

Safety and effectiveness in pediatric patients below the age of 18 years have not been established.

8.5 Geriatric Use

No overall differences in safety or effectiveness have been observed between elderly and other adult patients.

11 DESCRIPTION

Netarsudil is a Rho kinase inhibitor. Its chemical name is (S)-4-(3-amino-1-(isoquinolin-6-yl-amino)-1-oxopropan-2-yl) benzyl 2,4-dimethylbenzoate dimesylate. The molecular formula of the free base is C28H27N3O3 and the molecular formula of the dimesylate is C30H35N3O9S2. The molecular weight of the free base is 453.54 and the molecular weight of the dimesylate is 645.74. The chemical structure is:

Netarsudil dimesylate is a light yellow-to-white powder that is freely soluble in water, soluble in methanol, sparingly soluble in dimethyl formamide, and practically insoluble in dichloromethane and heptane.

RHOPRESSA (netarsudil ophthalmic solution) 0.02% is supplied as a sterile, isotonic, buffered aqueous solution of netarsudil dimesylate with a pH of approximately 5 and an osmolality of approximately 295 mOsmol/kg. It is intended for topical application in the eye. Each mL of RHOPRESSA contains 0.2 mg of netarsudil (equivalent to 0.28 mg of netarsudil dimesylate). Benzalkonium chloride, 0.015%, is added as a preservative. The inactive ingredients are: boric acid, mannitol, sodium hydroxide to adjust pH, and water for injection.

12 CLINICAL PHARMACOLOGY

12.1 Mechanism of Action

Netarsudil is a rho kinase inhibitor, which is believed to reduce IOP by increasing the outflow of aqueous humor through the trabecular meshwork. The exact mechanism is unknown.

12.3 Pharmacokinetics

Absorption

The systemic exposures of netarsudil and its active metabolite, AR-13503, were evaluated in 18 healthy subjects after topical ocular administration of RHOPRESSA 0.02% once daily (one drop bilaterally in the morning) for 8 days. There were no quantifiable plasma concentrations of netarsudil (lower limit of quantitation (LLOQ) 0.100 ng/mL) post dose on Day 1 and Day 8. Only one plasma concentration at 0.11 ng/mL for the active metabolite was observed for one subject on Day 8 at 8 hours post-dose.
Metabolism

After topical ocular dosing, netarsudil is metabolized by esterases in the eye.

13 NONCLINICAL TOXICOLOGY

13.1 Carcinogenesis, Mutagenesis, Impairment of Fertility

Long-term studies in animals have not been performed to evaluate the carcinogenic potential of netarsudil. Netarsudil was not mutagenic in the Ames test, in the mouse lymphoma test, or in the in vivo rat micronucleus test. Studies to evaluate the effects of netarsudil on male or female fertility in animals have not been performed.

14 CLINICAL STUDIES

RHOPRESSA 0.02% was evaluated in three randomized and controlled clinical trials, namely AR-13324-CS301 (NCT 02207491, referred to as Study 301), AR-13324-CS302 (NCT 02207621, referred to as Study 302), and AR-13324-CS304 (NCT 02558374, referred to as Study 304), in patients with open-angle glaucoma or ocular hypertension. Studies 301 and 302 enrolled subjects with baseline IOP lower than 27 mmHg and Study 304 enrolled subjects with baseline IOP lower than 30 mmHg. The treatment duration was 3 months in Study 301, 12 months in Study 302, and 6 months in Study 304.

The three studies demonstrated up to 5 mmHg reductions in IOP for subjects treated with RHOPRESSA 0.02% once daily in the evening. For patients with baseline IOP < 25 mmHg, the IOP reductions with RHOPRESSA 0.02% dosed once daily were similar to those with timolol 0.5% dosed twice daily (see Table 1). For patients with baseline IOP equal to or above 25 mmHg, however, RHOPRESSA 0.02% resulted in smaller mean IOP reductions at the morning time points than timolol 0.5% for study visits on Days 43 and 90; the difference in mean IOP reduction between the two treatment groups was as high as 3 mmHg, favoring timolol.

Table 1: Mean IOP Change from Baseline of Study Eye (mmHg) by Visit and Time

This table was produced based on the observed data from all randomized subjects who did not have major protocol violations. The treatment differences and two-sided CIs for comparing Rhopressa QD vs Timolol BID 0.5% were based on Analysis of Covariance (ANCOVA) adjusted for baseline IOP.

16 HOW SUPPLIED/STORAGE AND HANDLING

RHOPRESSA® (netarsudil ophthalmic solution) 0.02% (0.2 mg per mL) is supplied sterile in opaque white low density polyethylene bottles and tips with white polypropylene caps.

2.5 mL fill in a 4 mL container
NDC # 70727-497-25

Storage: Store at 2°C to 8°C (36°F to 46°F) until opened. After opening, the product may be kept at 2°C to 25°C (36°F to 77°F) for up to 6 weeks. If after opening the product is kept refrigerated at 2°C to 8°C (36°F to 46°F), then the product can be used until the expiration date stamped on the bottle. During shipment, the bottle may be maintained at temperatures up to 40°C (104°F) for a period not exceeding 14 days.

17 PATIENT COUNSELING INFORMATION

Handling the Container

Instruct patients to avoid allowing the tip of the dispensing container to contact the eye, surrounding structures, fingers, or any other surface in order to minimize contamination of the solution. Serious damage to the eye and subsequent loss of vision may result from using contaminated solutions [see Warnings and Precautions (5.2)].

When to Seek Physician Advice

Advise patients that if they develop an intercurrent ocular condition (e.g., trauma, infection, or decreased vision with or without eye pain), have ocular surgery, or develop any ocular reactions, particularly conjunctivitis and eyelid reactions, they should immediately seek their physician’s advice concerning the continued use of RHOPRESSA.

Use with Contact Lenses

Advise patients that RHOPRESSA contains benzalkonium chloride, which may be absorbed by soft contact lenses. Contact lenses should be removed prior to instillation of RHOPRESSA and may be reinserted 15 minutes following its administration.

Use with Other Ophthalmic Drugs

Advise patients that if more than one topical ophthalmic drug is being used, the drugs should be administered at least 5 minutes between applications.

Missed Dose

Advise patients that if one dose is missed, treatment should continue with the next dose in the evening.

© 2024 Alcon Inc.

U.S. Pat.: www.alconpatents.com
ALCON LABORATORIES, INC.
6201 South Freeway Fort Worth, Texas 76134 USA
1-800-757-9195
Alcon.medinfo@alcon.com

PACKAGE/LABEL PRINCIPAL DISPLAY PANEL

NDC 70727-497-25
rhopressa®
(netarsudil ophthalmic
solution) 0.02%
For topical application
in the eye
Sterile
Rx only
2.5 mL
Alcon
Usual dosage:
One drop in the affected
eye(s) once daily in the
evening.
Each mL Rhopressa®
ophthalmic solution contains:
Active: netarsudil mesylate
0.285 mg
Preservative:
benzalkonium chloride
0.15 mg
Inactives: mannitol, boric
acid, sodium hydroxide to
adjust pH and water for
injection.
Manufactured for:
ALCON LABORATORIES, INC.
Fort Worth, TX 76134 USA
U.S. Pat: www.alconpatents.com
Store at 2°C - 8°C
(36°F - 46°F) until opened.
After opening, the product
may be kept at 2°C - 25°C
(36°F - 77°F) for up to 6
weeks. If after opening the
product is kept refrigerated at
2°C - 8°C (36°F - 46°F), then
the product can be used until
the expiration date stamped
on the bottle. During
shipment, the bottle may be
maintained at temperatures
up to 40°C (104°F) for a
period not exceeding 14 days.
41079

NDC 70727-497-25 For topical application in the eye.
rhopressa®
(netarsudil ophthalmic
solution) 0.02%
Rx only
Sterile
2.5 mL Alcon 41077
See carton for storage conditions.
Manufactured for:
Alcon Laboratories, Inc.
Fort Worth, TX 76134
LOT:
EXP:

NDC 70727-497-99
SAMPLE - Not for Resale
rhopressa®
(netarsudil ophthalmic
solution) 0.02%
For topical application in the eye
Sterile Rx only
2.5 mL
Alcon
Usual dosage:
One drop in the affected
eye(s) once daily in the
evening.
Each mL Rhopressa®
ophthalmic solution contains:
Active: netarsudil mesylate
0.285 mg
Preservative:
benzalkonium chloride
0.15 mg
Inactives: mannitol, boric
acid, sodium hydroxide to
adjust pH and water for
injection.
Manufactured for:
ALCON LABORATORIES, INC.
Fort Worth, TX 76134 USA
U.S. Pat: www.alconpatents.com
Store at 2°C - 8°C
(36°F - 46°F) until opened.
After opening, the product
may be kept at 2°C - 25°C
(36°F - 77°F) for up to 6
weeks. If after opening the
product is kept refrigerated at
2°C - 8°C (36°F - 46°F), then
the product can be used until
the expiration date stamped
on the bottle. During
shipment, the bottle may be
maintained at temperatures
up to 40°C (104°F) for a
period not exceeding 14 days.
41080

NDC 70727-497-99 SAMPLE - Not for Resale For topical application in the eye.
rhopressa®
(netarsudil ophthalmic
solution) 0.02%
Rx only
Sterile
2.5 mL Alcon 41078
See carton for
storage conditions.
Manufactured for:
Alcon Laboratories, Inc.
Fort Worth, TX 76134
LOT:
EXP:

NDC 70727-497-25
rhopressa®
(netarsudil ophthalmic
solution) 0.02%
For topical application
in the eye
Sterile
Rx only 2.5 mL
Alcon
Usual dosage:
One drop in the affected eye(s) once
daily in the evening.
Each mL Rhopressa® ophthalmic solution
contains:
Active: netarsudil mesylate 0.285 mg
Preservative:
benzalkonium chloride
0.15 mg
Inactives: mannitol, boric acid, sodium
hydroxide toadjust pH and water for
injection.
ALCON LABORATORIES, INC.
Fort Worth, TX 76134 USA
U.S. Pat: www.alconpatents.com
Store at 2°C - 8°C (36°F - 46°F) until
opened. After opening, the product may
be kept at 2°C - 25°C (36°F - 77°F) for up
to 6 weeks. If after opening the product is
kept refrigerated at 2°C - 8°C (36°F - 46°F),
then the product can be used until the
expiration date stamped on the bottle.
During shipment, the bottle may be
maintained at temperatures up to 40°C
(104°F) for a period not exceeding 14 days.
300069021-1224

NDC 70727-497-25 For topical application in the eye.
rhopressa®
(netarsudil ophthalmic
solution) 0.02%
Rx only
Sterile
2.5 mL Alcon
See carton for storage conditions.
Alcon Laboratories, Inc.
Fort Worth, TX 76134
LOT: EXP.:
300069075
1224

PACKAGE/LABEL PRINCIPAL DISPLAY PANEL

NDC 70727-497-99
SAMPLE - Not for Resale
rhopressa®
(netarsudil ophthalmic
solution) 0.02%
For topical application
in the eye
Sterile
Rx only 2.5 mL
Alcon
Usual dosage:
One drop in the affected
eye(s) once daily in the
evening.
Each mL Rhopressa®
ophthalmic solution contains:
Active: netarsudil mesylate
0.285 mg
Preservative:
benzalkonium chloride
0.15 mg
Inactives: mannitol, boric
acid, sodium hydroxide to
adjust pH and water for
injection.
ALCON LABORATORIES, INC.
Fort Worth, TX 76134 USA
U.S. Pat: www.alconpatents.com
Store at 2°C - 8°C
(36°F - 46°F) until opened.
After opening, the product may
be kept at 2°C - 25°C
(36°F - 77°F) for up to 6 weeks.
If after opening the product is
kept refrigerated at 2°C - 8°C
(36°F - 46°F), then the product
can be used until the
expiration date stamped on the
bottle. During shipment, the
bottle may be maintained at
temperatures up to 40°C
(104°F) for a period not
exceeding 14 days.
300069020-1124

NDC 70727-497-99 SAMPLE - Not for Resale For topical application in the eye.
rhopressa®
(netarsudil ophthalmic
solution) 0.02%
Rx only
Sterile 2.5 mL Alcon
See carton for
storage conditions.
Alcon Laboratories, Inc.
Fort Worth, TX 76134 USA
LOT: EXP.:
300069074
1124